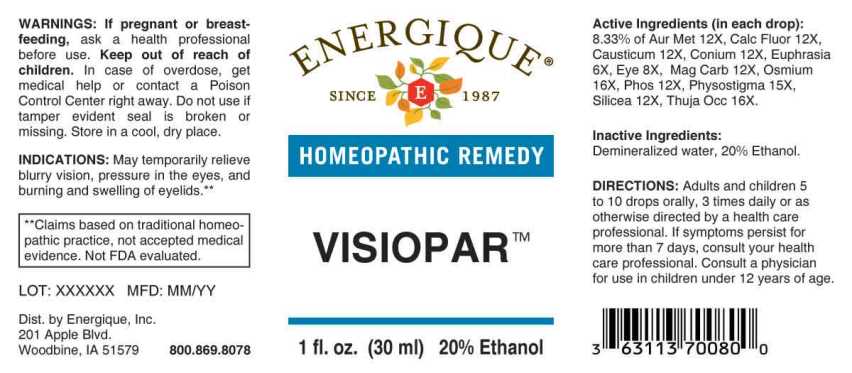 DRUG LABEL: Visiopar
NDC: 44911-0559 | Form: LIQUID
Manufacturer: Energique, Inc.
Category: homeopathic | Type: HUMAN OTC DRUG LABEL
Date: 20240419

ACTIVE INGREDIENTS: EUPHRASIA STRICTA 6 [hp_X]/1 mL; SUS SCROFA EYE 8 [hp_X]/1 mL; GOLD 12 [hp_X]/1 mL; CALCIUM FLUORIDE 12 [hp_X]/1 mL; CAUSTICUM 12 [hp_X]/1 mL; CONIUM MACULATUM FLOWERING TOP 12 [hp_X]/1 mL; MAGNESIUM CARBONATE 12 [hp_X]/1 mL; PHOSPHORUS 12 [hp_X]/1 mL; SILICON DIOXIDE 12 [hp_X]/1 mL; PHYSOSTIGMA VENENOSUM SEED 15 [hp_X]/1 mL; OSMIUM 16 [hp_X]/1 mL; THUJA OCCIDENTALIS LEAFY TWIG 16 [hp_X]/1 mL
INACTIVE INGREDIENTS: WATER; ALCOHOL

DRUG FACTS:

ACTIVE INGREDIENTS:

(in each drop): 8.33% of Aurum Metallicum 12X, Calcarea Fluorica 12X, Causticum 12X, Conium Maculatum 12X, Euphrasia Officinalis 6X, Eye (Suis) 8X, Magnesia Carbonica 12X, Osmium Metallicum 16X, Phosphorus 12X, Physostigma Venenosum 15X, Silicea 12X, Thuja Occidentalis 16X.

INDICATIONS:

May temporarily relieve minor inflammation and pressure in the eyes and burning and swelling of the eyelids.**

**Claims based on traditional homeopathic practice, not accepted medical evidence. Not FDA evaluated.

WARNINGS:

If pregnant or breast-feeding, ask a health professional before use.

Keep out of reach of children. In case of overdose, get medical help or contact a Poison Control Center right away.

Do not use if tamper evident seal is broken or missing. Store in a cool, dry place.

Keep out of reach of children. In case of overdose, get medical help or contact a Poison Control Center right away.

DIRECTIONS:

Adults and children 5 to 10 drops orally, 3 times daily or as otherwise directed by a health care professional. If symptoms persist for more than 7 days, consult your health care professional. Consult a physician for use in children under 12 years of age.

INDICATIONS:

May temporarily relieve minor inflammation and pressure in the eyes and burning and swelling of the eyelids.**

**Claims based on traditional homeopathic practice, not accepted medical evidence. Not FDA evaluated.

INACTIVE INGREDIENTS:

Demineralized water, 20% Ethanol.

QUESTIONS:

Dist. by Energique, Inc.
201 Apple Blvd
Woodbine, IA 51579 800.869.8078

PACKAGE LABEL DISPLAY:

ENERGIQUE

SINCE 1987

HOMEOPATHIC REMEDY

VISIOPAR

1 fl. oz. (30 ml)